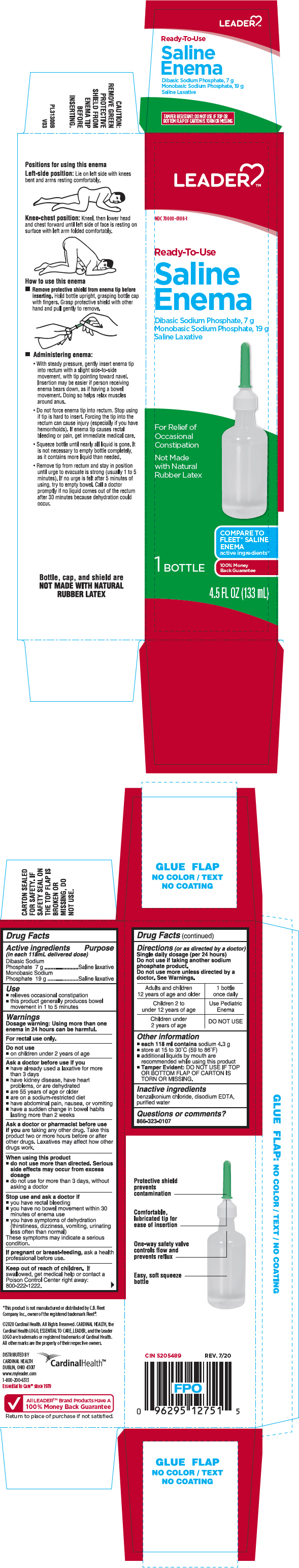 DRUG LABEL: Leader Ready to Use Saline 
NDC: 70000-0108 | Form: ENEMA
Manufacturer: Cardinal Health
Category: otc | Type: HUMAN OTC DRUG LABEL
Date: 20250929

ACTIVE INGREDIENTS: Sodium Phosphate, Dibasic, Unspecified Form 7 g/118 mL; Sodium Phosphate, Monobasic, Unspecified Form 19 g/118 mL
INACTIVE INGREDIENTS: Benzalkonium Chloride; Edetate Disodium Anhydrous; Water

Leader™ Ready to Use Saline Enema
Laxative

Drug Facts

ACTIVE INGREDIENT

Active ingredients (in each 118mL delivered dose) | Purpose
Dibasic Sodium Phosphate 7 g | Saline laxative
Monobasic Sodium Phosphate 19 g | Saline laxative

Use

- relieves occasional constipation
- this product generally produces bowel movement in 1 to 5 minutes

Warnings

Dosage warning

Using more than one enema in 24 hours can be harmful.

For rectal use only.

Do not use

- on children under 2 years of age

Ask a doctor before use if you

- have already used a laxative for more than 3 days
- have kidney disease, have heart problems, or are dehydrated
- are 55 years of age or older
- are on a sodium-restricted diet
- have abdominal pain, nausea, or vomiting
- have a sudden change in bowel habits lasting more than 2 weeks

Ask a doctor or pharmacist before use if you are taking any other drug. Take this product two or more hours before or after other drugs. Laxatives may affect how other drugs work.

When using this product

- do not use more than directed. Serious side effects may occur from excess dosage
- do not use for more than 3 days, without asking a doctor

Stop use and ask a doctor if

- you have rectal bleeding
- you have no bowel movement within 30 minutes of enema use
- you have symptoms of dehydration (thirstiness, dizziness, vomiting, urinating less often than normal)

These symptoms may indicate a serious condition.

PREGNANCY OR BREAST FEEDING

If pregnant or breast-feeding, ask a health professional before use.

Keep out of reach of children. If swallowed, get medical help or contact a Poison Control Center right away: 800-222-1222.

Directions (or as directed by a doctor)

Single daily dosage (per 24 hours)

Do not use if taking another sodium phosphate product.

Do not use more unless directed by a doctor. See Warnings.

Adults and children 12 years of age and older | 1 bottle once daily
Children 2 to under 12 years of age | Use Pediatric Enema
Children under 2 years of age | DO NOT USE

Other information

- each 118 ml contains sodium 4.3 g
- store at 15 to 30°C (59 to 86°F)
- additional liquids by mouth are recommended while using this product
- Tamper Evident: DO NOT USE IF TOP OR BOTTOM FLAP OF CARTON IS TORN OR MISSING.

Inactive ingredients

benzalkonium chloride, disodium EDTA, purified water

Questions or comments?

866-323-0107

DISTRIBUTED BY
CARDINAL HEALTH
DUBLIN, OHIO 43017

PRINCIPAL DISPLAY PANEL - 133 mL Bottle Carton

LEADER ™

NDC 70000-0108-1

Ready-To-Use

Saline
Enema
Dibasic Sodium Phosphate, 7 g
Monobasic Sodium Phosphate, 19 g
Saline Laxative

For Relief of
Occasional
Constipation

Not Made
with Natural
Rubber Latex

COMPARE TO
FLEET® SALINE
ENEMA
active ingredients*

1 BOTTLE

100% Money
Back Guarantee

4.5 FL OZ (133 mL)